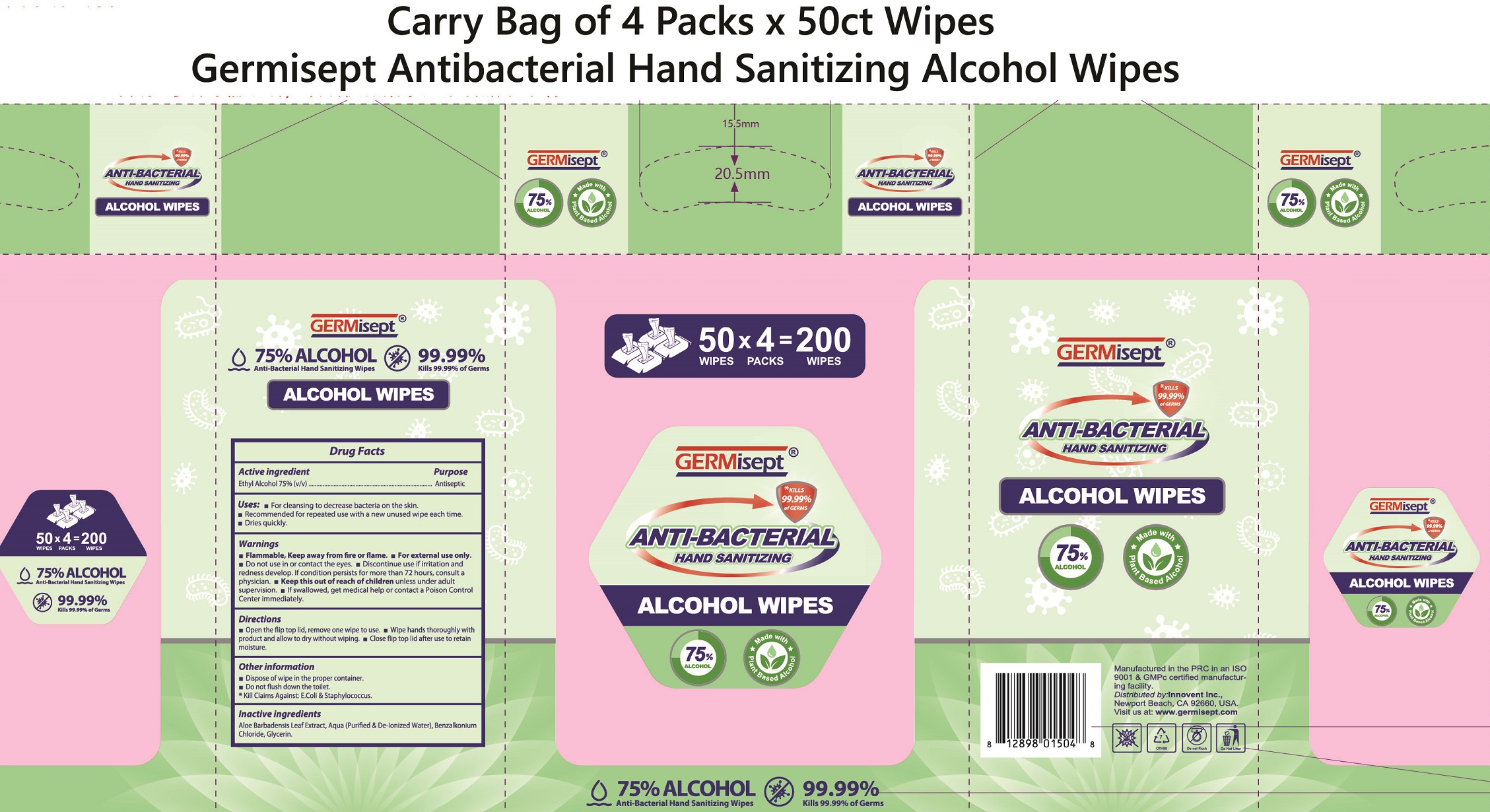 DRUG LABEL: GERMisept Antibacterial Hand Sanitizing Alcohol Wipes
NDC: 70335-011 | Form: CLOTH
Manufacturer: Innovent Inc
Category: otc | Type: HUMAN OTC DRUG LABEL
Date: 20231221

ACTIVE INGREDIENTS: ALCOHOL 75 mL/100 mL
INACTIVE INGREDIENTS: ALOE VERA LEAF; WATER; BENZALKONIUM CHLORIDE; GLYCERIN

GERMisept Anti-bacterial Hand Sanitizing Alcohol Wipes

Active ingredient

Ethyl Alcohol 75%(v/v)

Purpose

Antiseptic

Uses

- For cleansing to decrease bacteria on skin.
- Recommended for repeated use with a new unused wipe each time.
- Dries quickly.

Warnings

- Flammable, Keep away from fire or flame.
- For external use only.

Do not use

- in or contact the eyes.
- Discontinue use if irritation and redness develop. If condition persists for more than 72 hours, consult a physician.

Keep this out of reach of children

- unless under adult supervision.
- If swallowed, get medical help or contact a Poison Control Center immediately.

Directions

- Open the top cover, and tear the top sealing
- Pick wipe from center of roll, and thread wipe through the center of lid. Pull wipes to use.
- Wipe hands thoroughly with product and allow to dry without wiping.
- Close lid after use to retain moisture.

Other information

- Dispose of wipe in the proper container.
- Do not flush down the toilet.

*Kill Claims Against: E.Coli & Staphylococcus

Inactive ingredients

Aloe Barbadensis Leaf Extract, Aqua (Purified & De-Ionized Water), Benzalkonium Chloride, Glycerin.